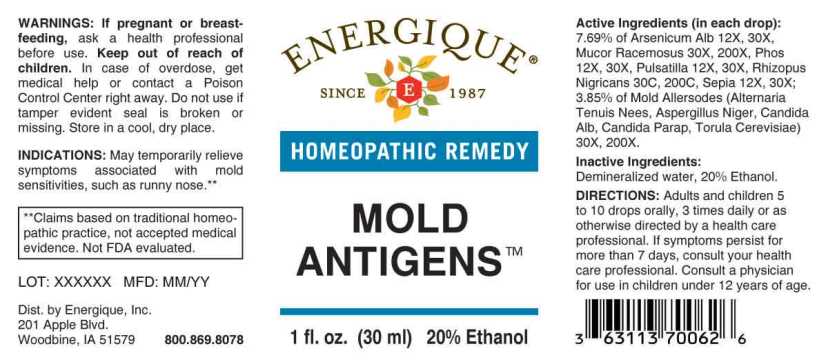 DRUG LABEL: Mold Antigens
NDC: 44911-0548 | Form: LIQUID
Manufacturer: Energique, Inc.
Category: homeopathic | Type: HUMAN OTC DRUG LABEL
Date: 20231213

ACTIVE INGREDIENTS: ALTERNARIA ALTERNATA 30 [hp_X]/1 mL; ASPERGILLUS NIGER VAR. NIGER 30 [hp_X]/1 mL; CANDIDA ALBICANS 30 [hp_X]/1 mL; CANDIDA PARAPSILOSIS 30 [hp_X]/1 mL; SACCHAROMYCES CEREVISIAE 30 [hp_X]/1 mL; MUCOR RACEMOSUS 30 [hp_X]/1 mL; ARSENIC TRIOXIDE 12 [hp_X]/1 mL; PHOSPHORUS 12 [hp_X]/1 mL; PULSATILLA PRATENSIS WHOLE 12 [hp_X]/1 mL; SEPIA OFFICINALIS JUICE 12 [hp_X]/1 mL; RHIZOPUS STOLONIFER 30 [hp_C]/1 mL
INACTIVE INGREDIENTS: WATER; ALCOHOL

Drug Facts:

ACTIVE INGREDIENTS:

(in each drop): 7.69% of Arsenicum Album 12X, 30X, Mucor Racemosus 30X, 200X, Phosphorus 12X, 30X, Pulsatilla 12X, 30X, Rhizopus Nigricans 30C, 200C, Sepia 12X, 30X; 3.85% of Alternaria Tenuis Nees 30X, 200X, Candida Albicans 30X, 200X, Candida Parapsilosis 30X, 200X, Torula Cerevisiae 30X, 200X.

INDICATIONS:

May temporarily relieve symptoms associated with mold allergies, such as runny nose.**

**Claims based on traditional homeopathic practice, not accepted medical evidence. Not FDA evaluated.

WARNINGS:

If pregnant or breast-feeding, ask a health professional before use.

Keep out of reach of children. In case of overdose, get medical help or contact a Poison Control Center right away.

Do not use if tamper evident seal is broken or missing. Store in a cool, dry place.

Keep out of reach of children. In case of overdose, get medical help or contact a Poison Control Center right away.

DIRECTIONS:

Adults and children 5 to 10 drops orally, 3 times daily or as otherwise directed by a health care professional. If symptoms persist, consult your health care professional. Consult a physician for use in children under 12 years of age.

INDICATIONS:

May temporarily relieve symptoms associated with mold allergies, such as runny nose.**

**Claims based on traditional homeopathic practice, not accepted medical evidence. Not FDA evaluated.

ACTIVE INGREDIENTS:

Demineralized water, 20% Ethanol.

QUESTIONS:

Dist. by Energique, Inc.

201 Apple Blvd

Woodbine, IA 51579 800.869.8078

PACKAGE LABEL DISPLAY:

ENERGIQUE

SINCE 1987

HOMEOPATHIC REMEDY

MOLD

ANTIGENS

1 fl. oz. (30 ml)